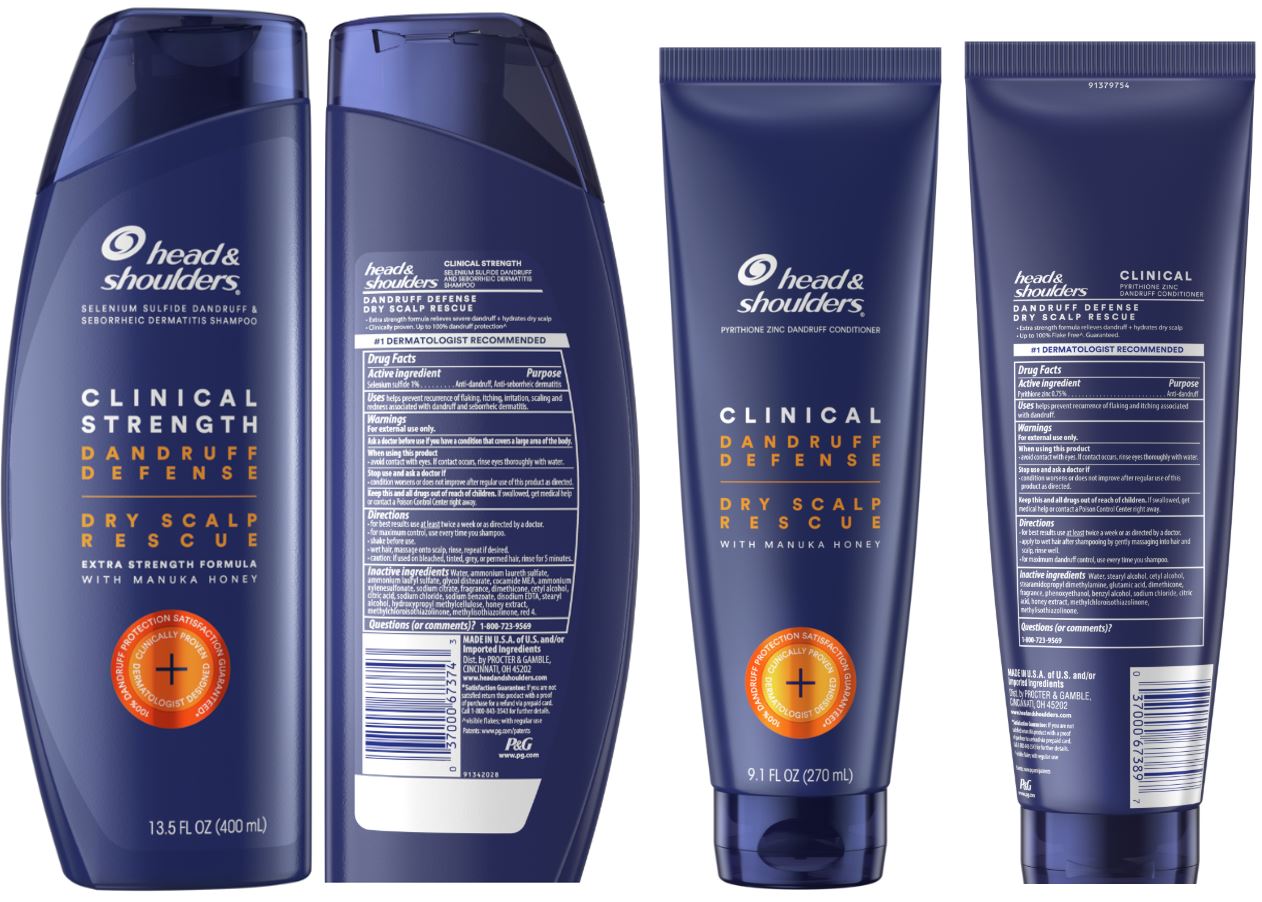 DRUG LABEL: Head and Shoulders Clinical Dry Scalp Rescue Kit
NDC: 69423-673 | Form: KIT | Route: TOPICAL
Manufacturer: The Procter & Gamble Manufacturing Company
Category: otc | Type: HUMAN OTC DRUG LABEL
Date: 20251231

ACTIVE INGREDIENTS: SELENIUM SULFIDE 1 g/100 mL; PYRITHIONE ZINC 0.75 g/100 mL
INACTIVE INGREDIENTS: HYPROMELLOSE, UNSPECIFIED; WATER; GLYCOL DISTEARATE; SODIUM CHLORIDE; SODIUM XYLENESULFONATE; COCAMIDOPROPYL BETAINE; DIMETHICONE; SODIUM BENZOATE; SODIUM CITRATE; CITRIC ACID MONOHYDRATE; HONEY; EDETATE SODIUM; SODIUM LAURYL SULFATE; FD&C RED NO. 4; STEARYL ALCOHOL; WATER; CETYL ALCOHOL; STEARAMIDOPROPYL DIMETHYLAMINE; GLUTAMIC ACID; PHENOXYETHANOL; BENZYL ALCOHOL; SODIUM CHLORIDE; METHYLISOTHIAZOLINONE; DIMETHICONE; CITRIC ACID MONOHYDRATE; METHYLCHLOROISOTHIAZOLINONE; HONEY; COCONUT

Head and Shoulders® Clinical Dry Scalp Rescue Kit

head & shoulders
CLINICAL STRENGTH SHAMPOO

DANDRUFF DEFENSE

DRY SCALP RESCUE

Drug Facts

Active ingredient

Selenium Sulfide 1%

Purpose

Anti-dandruff

Uses

helps prevent recurrence of flaking and itching associated with dandruff.

Warnings

For external use only.

When using this product

- avoid contact with eyes. If contact occurs, rinse eyes thoroughly with water.

Stop use and ask a doctor if

- condition worsens or does not improve after regular use of this product as directed.

KEEP OUT OF REACH OF CHILDREN

Keep this and all drugs out of reach of children.

If swallowed, get medical help or contact a Poison Control Center right away.

Directions

- for best results use at least twice a week or as directed by a doctor.
- for maximum dandruff control, use every time you shampoo.
- shake before use.
- wet hair, massage onto scalp, rinse, repeat if desired.

Inactive ingredients

sodium lauryl sulfate, glycol distearate, sodiumchloride, cocamidopropyl betaine, sodiumcitrate, sodiumxylenesulfonate, fragrance, dimethicone, citric acid, sodium benzoate, tetrasodiumEDTA, hydroxypropylmethylcellulose, honey extract, red 4.

Questions (or comments)?

1-800-723-9569

head & shoulders
CLINICAL STRENGTH CONDITIONER

DANDRUFF DEFENSE

DRY SCALP RESCUE

Drug Facts

Active ingredient

Pyrithione zinc 0.5%

Purpose

Anti-dandruff

Uses

helps prevent recurrence of flaking and itching associated with dandruff.

Warnings

For external use only.

When using this product

- avoid contact with eyes. If contact occurs, rinse eyes thoroughly with water.

Stop use and ask a doctor if

- condition worsens or does not improve after regular use of this product as directed.

KEEP OUT OF REACH OF CHILDREN

Keep this and all drugs out of reach of children.

If swallowed, get medical help or contact a Poison Control Center right away.

Directions

- for best results use at least twice a week or as directed by a doctor.
- apply to wet hair after shampooing by gently massaging into hair and scalp, rinse well.

Inactive ingredients

Water, stearyl alcohol, cetyl alcohol, stearamidopropyl dimethylamine, glutamic acid, dimethicone, fragrance, phenoxyethanol, benzyl alcohol,sodium chloride, citric acid, honey extract, methylchloroisothiazolinone, methylisothiazolinone

Questions (or comments)?

1-800-723-9569

Dist. by PROCTER & GAMBLE,
CINCINNATI, OH 45202

PRINCIPAL DISPLAY PANEL - Kit

head & shoulders ®

Shampoo & Conditioner

head & shoulders ®

selenium sulfide dandruff & soborrheic dermatitis shampoo

CLINICAL STRENGTH

DANDRUFF DEFENSE

DRY SCALP

RESCUE

head & shoulders ®

pyrithione zinc dandruff conditioner

CLINICAL STRENGTH

DANDRUFF DEFENSE

DRY SCALP

RESCUE

1 SELENIUM SULFIDE DANDRUFF & SEBORRHEIC DERMATITIS

SHAMPOO 13.5 FL OZ (400 mL)

1 PYRITHIONE ZINC DANDRUFF

CONDITIONER 9.1 FL OZ (270 mL)